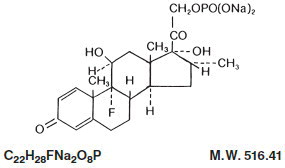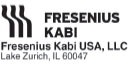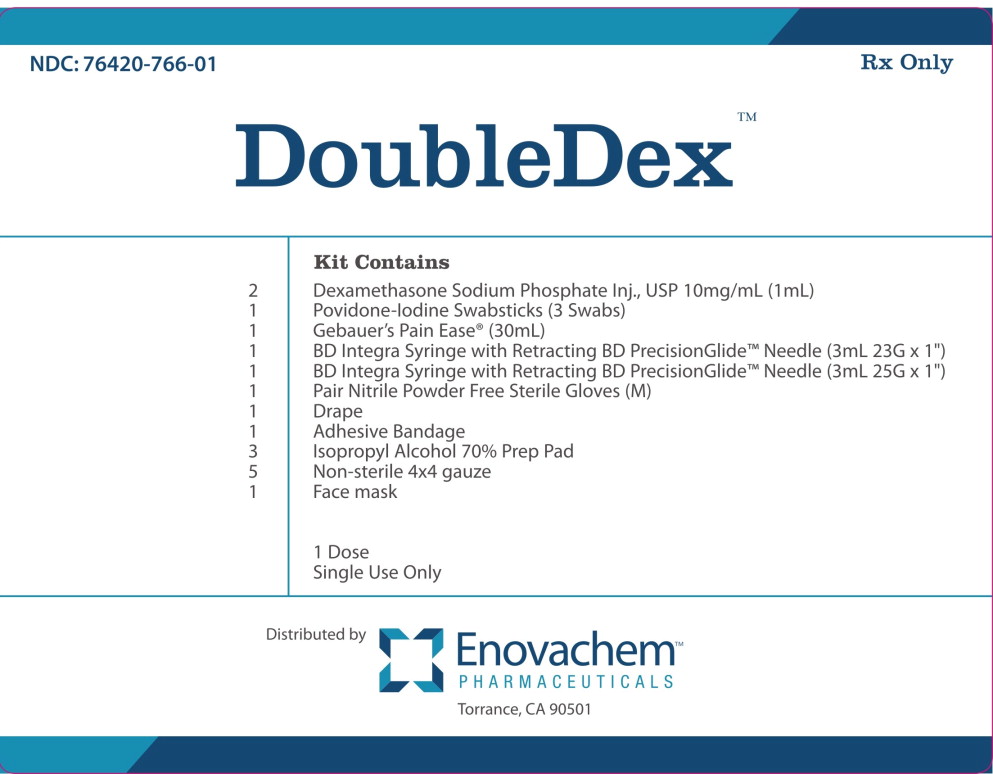 DRUG LABEL: DoubleDex Kit
NDC: 76420-766 | Form: KIT | Route: INTRAMUSCULAR
Manufacturer: Asclemed USA, Inc.
Category: prescription | Type: HUMAN PRESCRIPTION DRUG LABEL
Date: 20260108

ACTIVE INGREDIENTS: DEXAMETHASONE SODIUM PHOSPHATE 10 mg/1 mL; POVIDONE-IODINE 10 mg/1 mL; ISOPROPYL ALCOHOL 70 mL/100 mL
INACTIVE INGREDIENTS: SODIUM CITRATE; CITRIC ACID MONOHYDRATE; SODIUM HYDROXIDE; GLYCERIN; POLYSORBATE 80; SODIUM CITRATE; SODIUM PHOSPHATE, DIBASIC, ANHYDROUS; CITRIC ACID ACETATE; WATER; WATER

Dexamethasone Sodium Phosphate Injection, USP

For Intravenous or Intramuscular Use Only

Rx only

DESCRIPTION

Dexamethasone Sodium Phosphate Injection, USP, is a water-soluble inorganic ester of dexamethasone which produces a rapid response even when injected intramuscularly.

Dexamethasone Sodium Phosphate, USP chemically is Pregna-1,4-diene-3,20-dione, 9-fluoro- 11,17-dihydroxy-16-methyl-21-(phosphonooxy)-, disodium salt, (11ß, 16α).

It occurs as a white to creamy white powder, is exceedingly hygroscopic, is soluble in water and its solutions have a pH between 7.0 and 8.5. It has the following structural formula:

Each mL of Dexamethasone Sodium Phosphate Injection, USP (Preservative Free) contains dexamethasone sodium phosphate, USP equivalent to 10 mg dexamethasone phosphate; 24.75 mg sodium citrate, dihydrate; and Water for Injection, q.s. pH adjusted with citric acid or sodium hydroxide, if necessary. pH: 7.0 to 8.5.

CLINICAL PHARMACOLOGY

Dexamethasone sodium phosphate injection has a rapid onset but short duration of action when compared with less soluble preparations. Because of this, it is suitable for the treatment of acute disorders responsive to adrenocortical steroid therapy.

Naturally occurring glucocorticoids (hydrocortisone and cortisone), which also have salt-retaining properties, are used as replacement therapy in adrenocortical deficiency states. Their synthetic analogs, including dexamethasone, are primarily used for their potent anti-inflammatory effects in disorders of many organ systems.

Glucocorticoids cause profound and varied metabolic effects. In addition, they modify the body’s immune responses to diverse stimuli.

At equipotent anti-inflammatory doses, dexamethasone almost completely lacks the sodium-retaining property of hydrocortisone and closely related derivatives of hydrocortisone.

INDICATIONS AND USAGE

By intravenous or intramuscular injection when oral therapy is not feasible:

1. Endocrine Disorders

Primary or secondary adrenocortical insufficiency (hydrocortisone or cortisone is the drug of choice; synthetic analogs may be used in conjunction with mineralocorticoids

where applicable; in infancy, mineralocorticoid supplementation is of particular importance).

Acute adrenocortical insufficiency (hydrocortisone or cortisone is the drug of choice; mineralocorticoid supplementation may be necessary, particularly when synthetic analogs

are used).

Preoperatively, and in the event of serious trauma or illness, in patients with known adrenal insufficiency or when adrenocortical reserve is doubtful.

Shock unresponsive to conventional therapy if adrenocortical insufficiency exists or is suspected.

Congenital adrenal hyperplasia

Nonsuppurative thyroiditis

Hypercalcemia associated with cancer

2. Rheumatic Disorders

As adjunctive therapy for short-term administration (to tide the patient over an acute episode or exacerbation) in:

Post-traumatic osteoarthritis

Synovitis of osteoarthritis

Rheumatoid arthritis, including juvenile rheumatoid arthritis (selected cases may require low-dose maintenance therapy).

Acute and subacute bursitis

Epicondylitis

Acute nonspecific tenosynovitis

Acute gouty arthritis

Psoriatic arthritis

Ankylosing spondylitis

3. Collagen Diseases

During an exacerbation or as maintenance therapy in selected cases of:

Systemic lupus erythematosus

Acute rheumatic carditis

4. Dermatologic Diseases

Pemphigus

Severe erythema multiforme (Stevens-Johnson syndrome)

Exfoliative dermatitis

Bullous dermatitis herpetiformis

Severe seborrheic dermatitis

Severe psoriasis

Mycosis fungoides

5. Allergic States

Control of severe or incapacitating allergic conditions intractable to adequate trials of conventional treatment in:

Bronchial asthma

Contact dermatitis

Atopic dermatitis

Serum sickness

Seasonal or perennial allergic rhinitis

Drug hypersensitivity reactions

Urticarial transfusion reactions

Acute noninfectious laryngeal edema (epinephrine is the drug of first choice).

6. Ophthalmic Diseases

Severe acute and chronic allergic and inflammatory processes involving the eye, such as:

Herpes zoster ophthalmicus

Iritis, iridocyclitis

Chorioretinitis

Diffuse posterior uveitis and choroiditis

Optic neuritis

Sympathetic ophthalmia

Anterior segment inflammation

Allergic conjunctivitis

Keratitis

Allergic corneal marginal ulcers

7. Gastrointestinal Diseases

To tide the patient over a critical period of the disease in:

Ulcerative colitis (systemic therapy)

Regional enteritis (systemic therapy)

8. Respiratory Diseases

Symptomatic sarcoidosis

Berylliosis

Fulminating or disseminated pulmonary tuberculosis when used concurrently with appropriate antituberculous chemotherapy.

Loeffler’s syndrome not manageable by other means.

Aspiration pneumonitis

9. Hematologic Disorders

Acquired (autoimmune) hemolytic anemia.

Idiopathic thrombocytopenic purpura in adults

(IV only; IM administration is contraindicated).

Secondary thrombocytopenia in adults

Erythroblastopenia (RBC anemia)

Congenital (erythroid) hypoplastic anemia

10. Neoplastic Diseases

For palliative management of:

Leukemias and lymphomas in adults

Acute leukemia of childhood

11. Edematous States

To induce diuresis or remission of proteinuria in the nephrotic syndrome, without uremia, of the idiopathic type or that due to lupus erythematosus.

12. Miscellaneous

Tuberculous meningitis with subarachnoid block or impending block when used concurrently with appropriate antituberculous chemotherapy.

Trichinosis with neurologic or myocardial involvement.

13. Diagnostic testing of adrenocortical hyperfunction.

14. Cerebral Edema associated with primary or metastatic brain tumor, craniotomy, or head injury. Use in cerebral edema is not a substitute for careful neurosurgical evaluation

and definitive management such as neurosurgery or other specific therapy.

CONTRAINDICATIONS

Systemic fungal infections (see WARNINGSregarding amphotericin B).

Hypersensitivity to any component of this product (see WARNINGS) .

WARNINGS

Because rare instances of anaphylactoid reactions have occurred in patients receiving parenteral corticosteroid therapy, appropriate precautionary measures should be taken prior to administration, especially when the patient has a history of allergy to any drug. Anaphylactoid and hypersensitivity reactions have been reported for dexamethasone sodium phosphate injection (see ADVERSE REACTIONS).

Corticosteroids may exacerbate systemic fungal infections and, therefore, should not be used in the presence of such infections unless they are needed to control drug reactions due to amphotericin B. Moreover, there have been cases reported in which concomitant use of amphotericin B and hydrocortisone was followed by cardiac enlargement and congestive failure.

In patients on corticosteroid therapy subjected to any unusual stress, increased dosage of rapidly acting corticosteroids before, during, and after the stressful situation is indicated.

Drug-induced secondary adrenocortical insufficiency may result from too rapid withdrawal of corticosteroids and may be minimized by gradual reduction of dosage. This type of relative insufficiency may persist for months after discontinuation of therapy; therefore, in any situation of stress occurring during that period, hormone therapy should be reinstituted. If the patient is receiving steroids already, dosage may have to be increased. Since mineralocorticoid secretion may be impaired, salt and/or a mineralocorticoid should be administered concurrently.

Corticosteroids may mask some signs of infection, and new infections may appear during their use. There may be decreased resistance and inability to localize infection when corticosteroids are used. Moreover, corticosteroids may affect the nitroblue-tetrazolium test for bacterial infection and produce false negative results.

In cerebral malaria, a double-blind trial has shown that the use of corticosteroids is associated with prolongation of coma and a higher incidence of pneumonia and gastrointestinal bleeding.

Corticosteroids may activate latent amebiasis. Therefore, it is recommended that latent or active amebiasis be ruled out before initiating corticosteroid therapy in any patient who has spent time in the tropics or in any patient with unexplained diarrhea.

Prolonged use of corticosteroids may produce posterior subcapsular cataracts, glaucoma with possible damage to the optic nerves, and may enhance the establishment of secondary ocular infections due to fungi or viruses.

Average and large doses of cortisone or hydrocortisone can cause elevation of blood pressure, salt and water retention, and increased excretion of potassium. These effects are less likely to occur with the synthetic derivatives except when used in large doses. Dietary salt restriction and potassium supplementation may be necessary. All corticosteroids increase calcium excretion.

Administration of live virus vaccines, including smallpox, is contraindicated in individuals receiving immunosuppressive doses of corticosteroids. If inactivated viral or bacterial vaccines are administered to individuals receiving immunosuppressive doses of corticosteroids, the expected serum antibody response may not be obtained. However, immunization procedures may be undertaken in patients who are receiving corticosteroids as replacement therapy, e.g., for Addison’s disease.

Patients who are on drugs which suppress the immune system are more susceptible to infections than healthy individuals. Chickenpox and measles, for example, can have a more serious or even fatal course in non-immune children or adults on corticosteroids. In such children or adults who have not had these diseases, particular care should be taken to avoid exposure. The risk of developing a disseminated infection varies among individuals and can be related to the dose, route and duration of corticosteroid administration as well as to the underlying disease. If exposed to chickenpox, prophylaxis with varicella zoster immune globulin (VZIG) may be indicated. If chickenpox develops, treatment with antiviral agents may be considered. If exposed to measles, prophylaxis with immune globulin (IG) may be indicated. (See the respective package inserts for VZIG and IG for complete prescribing information).

The use of dexamethasone sodium phosphate injection in active tuberculosis should be restricted to those cases of fulminating or disseminated tuberculosis in which the corticosteroid is used for the management of the disease in conjunction with an appropriate antituberculous regimen.

If corticosteroids are indicated in patients with latent tuberculosis or tuberculin reactivity, close observation is necessary as reactivation of the disease may occur. During prolonged corticosteroid therapy, these patients should receive chemoprophylaxis.

Literature reports suggest an apparent association between use of corticosteroids and left ventricular free wall rupture after a recent myocardial infarction; therefore, therapy with corticosteroids should be used with great caution in these patients.

Serious Neurologic Adverse Reactions with Epidural Administration

Serious neurologic events, some resulting in death, have been reported with epidural injection of corticosteroids. Specific events reported include, but are not limited to, spinal cord infarction, paraplegia, quadriplegia, cortical blindness, and stroke. These serious neurologic events have been reported with and without use of fluoroscopy. The safety and effectiveness of epidural administration of corticosteroids has not been established, and corticosteroids are not approved for this use.

Usage in Pregnancy

Since adequate human reproduction studies have not been done with corticosteroids, use of these drugs in pregnancy or in women of childbearing potential requires that the anticipated benefits be weighed against the possible hazards to the mother and embryo or fetus. Infants born of mothers who have received substantial doses of corticosteroids during pregnancy should be carefully observed for signs of hypoadrenalism.

Corticosteroids appear in breast milk and could suppress growth, interfere with endogenous corticosteroid production, or cause other unwanted effects. Mothers taking pharmacologic doses of corticosteroids should be advised not to nurse.

PRECAUTIONS

This product, like many other steroid formulations, is sensitive to heat. Therefore, it should not be autoclaved when it is desirable to sterilize the exterior of the vial.

Following prolonged therapy, withdrawal of corticosteroids may result in symptoms of the corticosteroid withdrawal syndrome including fever, myalgia, arthralgia, and malaise. This may occur in patients even without evidence of adrenal insufficiency.

There is an enhanced effect of corticosteroids in patients with hypothyroidism and in those with cirrhosis.

Corticosteroids should be used cautiously in patients with ocular herpes simplex for fear of corneal perforation.

The lowest possible dose of corticosteroid should be used to control the condition under treatment, and when reduction in dosage is possible, the reduction must be gradual.

Psychic derangements may appear when corticosteroids are used, ranging from euphoria, insomnia, mood swings, personality changes, and severe depression to frank psychotic manifestations. Also, existing emotional instability or psychotic tendencies may be aggravated by corticosteroids.

Aspirin should be used within caution in conjunction with corticosteroids in hypoprothrombinemia.

Steroids should be used with caution in nonspecific ulcerative colitis, if there is a probability of impending perforation, abscess, or other pyogenic infection, also in diverticulitis, fresh intestinal anastomoses, active or latent peptic ulcer, renal insufficiency, hypertension, osteoporosis, and myasthenia gravis. Signs of peritoneal irritation following gastrointestinal perforation in patients receiving large doses of corticosteroids may be minimal or absent. Fat embolism has been reported as a possible complication of hypercortisonism.

When large doses are given, some authorities advise that antacids be administered between meals to help prevent peptic ulcer.

Steroids may increase or decrease motility and number of spermatozoa in some patients.

Phenytoin, phenobarbital, ephedrine, and rifampin may enhance the metabolic clearance of corticosteroids resulting in decreased blood levels and lessened physiologic activity, thus requiring adjustment in corticosteroid dosage. These interactions may interfere with dexamethasone suppression tests which should be interpreted with caution during administration of these drugs.

False negative results in the dexamethasone suppression test (DST) in patients being treated with indomethacin have been reported. Thus, results of the DST should be interpreted with caution in these patients.

The prothrombin time should be checked frequently in patients who are receiving corticosteroids and coumarin anticoagulants at the same time because of reports that corticosteroids have altered the response to these anticoagulants. Studies have shown that the usual effect produced by adding corticosteroids is inhibition of response to coumarins, although there have been some conflicting reports of potentiation not substantiated by studies.

When corticosteroids are administered concomitantly with potassium-depleting diuretics, patients should be observed closely for development of hypokalemia.

The slower rate of absorption by intramuscular administration should be recognized.

Information for Patients

Susceptible patients who are on immunosuppressant doses of corticosteroids should be warned to avoid exposure to chickenpox or measles. Patients should also be advised that if they are exposed, medical advice should be sought without delay.

Pediatric Use

Growth and development of infants and children patients on prolonged corticosteroid therapy should be carefully followed.

ADVERSE REACTIONS

Fluid and electrolyte disturbances:

Sodium retention

Fluid retention

Congestive heart failure in susceptible patients

Potassium loss

Hypokalemic alkalosis

Hypertension

Musculoskeletal:

Muscle weakness

Steroid myopathy

Loss of muscle mass

Osteoporosis

Vertebral compression fractures

Aseptic necrosis of femoral and humeral heads

Tendon rupture

Pathologic fracture of long bones

Gastrointestinal:

Peptic ulcer with possible subsequent perforation and hemorrhage

Perforation of the small and large bowel; particularly in patients with inflammatory

bowel disease

Pancreatitis

Abdominal distention

Ulcerative esophagitis

Dermatologic:

Impaired wound healing

Thin fragile skin

Petechiae and ecchymoses

Erythema

Increased sweating

May suppress reactions to skin tests

Burning or tingling, especially in the perineal area (after IV injection)

Other cutaneous reactions, such as allergic dermatitis, urticaria, angioneurotic edema

Neurologic:

Convulsions

Increased intracranial pressure with papilledema (pseudotumor cerebri) usually after

treatment

Vertigo

Headache

Psychic disturbances

Endocrine:

Menstrual irregularities

Development of cushingoid state

Suppression of growth in pediatric patients

Secondary adrenocortical and pituitary unresponsiveness, particularly in times of

stress, as in trauma, surgery, or illness

Decreased carbohydrate tolerance

Manifestations of latent diabetes mellitus

Increased requirements for insulin or oral hypoglycemic agents in diabetics

Hirsutism

Ophthalmic:

Posterior subcapsular cataracts

Increased intraocular pressure

Glaucoma

Exophthalmos

Retinopathy of prematurity

Metabolic:

Negative nitrogen balance due to protein catabolism

Cardiovascular:

Myocardial rupture following recent myocardial infarction (see WARNINGS)

Hypertrophic cardiomyopathy in low birth weight infants

Other:

Anaphylactoid or hypersensitivity reactions

Thromboembolism

Weight gain

Increased appetite

Nausea

Malaise

Hiccups

The following additional adverse reactions are related to parenteral corticosteroid therapy:

Hyperpigmentation or hypopigmentation

Subcutaneous and cutaneous atrophy

Sterile abscess

Charcot-like arthropathy

OVERDOSAGE

Reports of acute toxicity and/or death following overdosage of glucocorticoids are rare. In the event of overdosage, no specific antidote is available; treatment is supportive and symptomatic.

The oral LD50 of dexamethasone in female mice was 6.5 g/kg. The intravenous LD50 of dexamethasone sodium phosphate in female mice was 794 mg/kg.

DOSAGE AND ADMINISTRATION

Dexamethasone sodium phosphate injection, 10 mg/mL– For intravenous and intramuscular injection only.

Dexamethasone sodium phosphate injection can be given directly from the vial, or it can be added to Sodium Chloride Injection or Dextrose Injection and administered by intravenous drip.

Solutions used for intravenous administration or further dilution of this product should be preservative free when used in the neonate, especially the premature infant.

When it is mixed with an infusion solution, sterile precautions should be observed. Since infusion solutions generally do not contain preservatives, mixtures should be used within 24 hours.

DOSAGE REQUIREMENTS ARE VARIABLE AND MUST BE INDIVIDUALIZED ON THE BASIS OF THE DISEASE AND THE RESPONSE OF THE PATIENT.

Intravenous and Intramuscular Injection

The initial dosage of dexamethasone sodium phosphate injection varies from 0.5 to 9 mg a day depending on the disease being treated. In less severe diseases doses lower than 0.5 mg may suffice, while in severe diseases doses higher than 9 mg may be required.

The initial dosage should be maintained or adjusted until the patient’s response is satisfactory. If a satisfactory clinical response does not occur after a reasonable period of time, discontinue dexamethasone sodium phosphate injection and transfer the patient to other therapy.

After a favorable initial response, the proper maintenance dosage should be determined by decreasing the initial dosage in small amounts to the lowest dosage that maintains an adequate clinical response.

Patients should be observed closely for signs that might require dosage adjustment, including changes in clinical status resulting from remissions or exacerbations of the disease, individual drug responsiveness, and the effect of stress (e.g., surgery, infection, trauma). During stress it may be necessary to increase dosage temporarily.

If the drug is to be stopped after more than a few days of treatment, it usually should be withdrawn gradually.

When the intravenous route of administration is used, dosage usually should be the same as the oral dosage. In certain overwhelming, acute, life-threatening situations, however, administration in dosages exceeding the usual dosages may be justified and may be in multiples of the oral dosages. The slower rate of absorption by intramuscular administration should be recognized.

Shock

There is a tendency in current medical practice to use high (pharmacologic) doses of corticosteroids for the treatment of unresponsive shock. The following dosages of dexamethasone sodium phosphate injection have been suggested by various authors:

Author | Dosage
Cavanagh^1 | 3 mg/kg of body weight per 24 hours by constant intravenous infusion after an initial intravenous injection of 20 mg
Dietzman^2 | 2 to 6 mg/kg of body weight as a single intravenous injection
Frank^3 | 40 mg initially followed by repeat intravenous injection every 4 to 6 hours while shock persists
Oaks^4 | 40 mg initially followed by repeat intravenous injection every 2 to 6 hours while shock persists
Schumer^5 | 1 mg/kg of body weight as a single intravenous injection

Administration of high dose corticosteroid therapy should be continued only until the patient’s condition has stabilized and usually not longer than 48 to 72 hours.

Although adverse reactions associated with high dose, short-term corticosteroid therapy are uncommon, peptic ulceration may occur.

Cerebral Edema

Dexamethasone sodium phosphate injection is generally administered initially in a dosage of 10 mg intravenously followed by four mg every six hours intramuscularly until the symptoms of cerebral edema subside. Response is usually noted within 12 to 24 hours and dosage may be reduced after two to four days and gradually discontinued over a period of five to seven days. For palliative management of patients with recurrent or inoperable brain tumors, maintenance therapy with 2 mg two or three times a day may be effective.

Acute Allergic Disorders

In acute, self-limited allergic disorders or acute exacerbations of chronic allergic disorders, the following dosage schedule combining parenteral and oral therapy is suggested:

Dexamethasone sodium phosphate injection, first day, 4 or 8 mg intramuscularly.

Dexamethasone tablets, 0.75 mg: second and third days, 4 tablets in two divided doses each day; fourth day, 2 tablets in two divided doses; fifth and sixth days, 1 tablet each day; seventh day, no treatment; eighth day, follow-up visit.

This schedule is designed to ensure adequate therapy during acute episodes, while minimizing the risk of overdosage in chronic cases.

Parenteral drug products should be inspected visually for particulate matter and discoloration prior to administration, whenever the solution and container permit.

HOW SUPPLIED

Dexamethasone Sodium Phosphate Injection, USP (Preservative Free) equivalent to 10 mg dexamethasone phosphate, is supplied in a single dose vial as follows:

Product; No. | NDC; No. | Strength | Vial Size
500601 | 63323-506-01 | 10 mg per mL | 1 mL vial, packaged in twenty-fives.

This container closure is not made with natural rubber latex.

Storage

Store at 20° to 25°C (68° to 77°F) [see USP Controlled Room Temperature]. Sensitive to heat. Do not autoclave.

Protect from freezing.

Protect from light.

Single dose vials–Store in container until time of use. Discard unused portion.

Multiple dose vials–Store in container until contents are used.

REFERENCES

1. Cavanagh, D.; Singh, K.B.: Endotoxin shock in pregnancy and abortion, in: “Corticosteroids in the Treatment of Shock”, Schumer, W.; Nyhus, L.M., Editors, Urbana, University of Illinois Press, 1970, pp. 86-96.
2. Dietzman, R.H.; Ersek, R.A.; Bloch, J.M.; Lilleheir, R.C.: High-output, low-resistance gram-negative septic shock in man, Angiology 20: 691-700, Dec. 1969.
3. Frank, E.: Clinical observations in shock and management (in: Shields, T.F., ed.: Symposium on current concepts and management of shock), J. Maine Med. Ass. 59: 195-200, Oct. 1968.
4. Oaks, W. W.; Cohen, H.E.: Endotoxin shock in the geriatric patient, Geriat. 22: 120-130, Mar. 1967.
5. Schumer, W.; Nyhus, L.M.: Corticosteroid effect on biochemical parameters of human oligemic shock, Arch. Surg. 100: 405-408, Apr. 1970.

45955E

Revised: May 2014

Active Ingredient Purpose

Povidone Iodine 10% w/v (9.85% w/w) Antiseptic

Purpose:

- First aid antiseptic to help prevent skin infection in minor cuts, scrapes and burns.
- For preparation of the skin prior to surgery.
- Helps reduce bacteria that can potentially cause skin infections.

Warnings:

- FOR EXTERNAL USE ONLY

Do not use:

- As a first aid antiseptic for more than 1 week.
- In the eyes.
- Over large areas of the body.

Ask a doctor before use if you have:

- Deep puncture wounds
- Animal bites
- Serious burns

Stop Use:

- If irritation and redness develop
- If condition persists for more than 72 hours, consult a physician.

Keep out of reach of children.If swallowed, get medical help or contact a Poison Control Center.

Directions Povidone iodine:

Tear at notch, remove applicator, use only once.

As a first aid antiseptic

- clean affected area
- apply 1 to 3 times daily
- may be covered with a sterile bandage, if bandaged let dry.

For preoperative patient skin preparation

- clean area
- apply to operative site prior to surgery using the applicator

Other information:

Store at room temperature.

Avoid excessive heat

INDICATIONS AND USAGE

For use as an

- first aid antiseptic
- pre-operative skin preperation

Inactive Ingredients

Inactive ingredients: Citric acid, glycerin, polysorbate 80, sodium citrate USP, sodium phosphate dibasic, water

Active ingredient

Isopropyl Alcohol 70% v/v

Purpose

Antiseptic

Uses

For first aid to decrease germs in

- minor cuts
- scrapes
- burns

For preparation of the skin prior to injection

Warnings

For external use only

Flammable - keep away from fire or flame

Do not use

with electrocautery procedures

When using this product do not

- get into eyes
- apply over large areas of the body
- in case of deep or puncture wounds, animal bites or serious burns consult a doctor

Stop use and ask a doctor if

- condition persists or gets worse or lasts for more than 72 hours
- do not use longer than 1 week unless directed by a doctor

Keep out of reach of children.

If swallowed, get medical help or contact a Poison Control Center right away.

Directions

- apply to skin as needed
- discard after single use

Other information

Protect from freezing and avoid excessive heat

Inactive ingredient

Water

PACKAGE LABEL

PRINCIPAL DISPLAY PANEL

NDC: 76420-766-01

RX Only

DoubleDex™

Kit Contains

2 Dexamethasone Sodium Phosphate Inj., USP 10mg/mL (1mL)

1 Povidone-Iodine Swabsticks (3 Swabs)

1 Gebauer's Pain Ease® (30mL)

1 BD Integra Syringe with Retracting BD PrecisionGlide™ Needle (3mL 23G x 1”)

1 BD Integra Syringe with Retracting BD PrecisionGlide™ Needle (3mL 25G x 1”)

1 Pair Nitrile Powder Free Sterile Gloves (M)

1 Drape

1 Adhesive Bandage

3 Isopropyl Alcohol 70% Prep Pads

5 Non-sterile 4x4 gauze

1 Face mask

1 Dose

Single Use Only

Distributed by

Enovachem™

PHARMACEUTICALS

Torrance, CA 90501